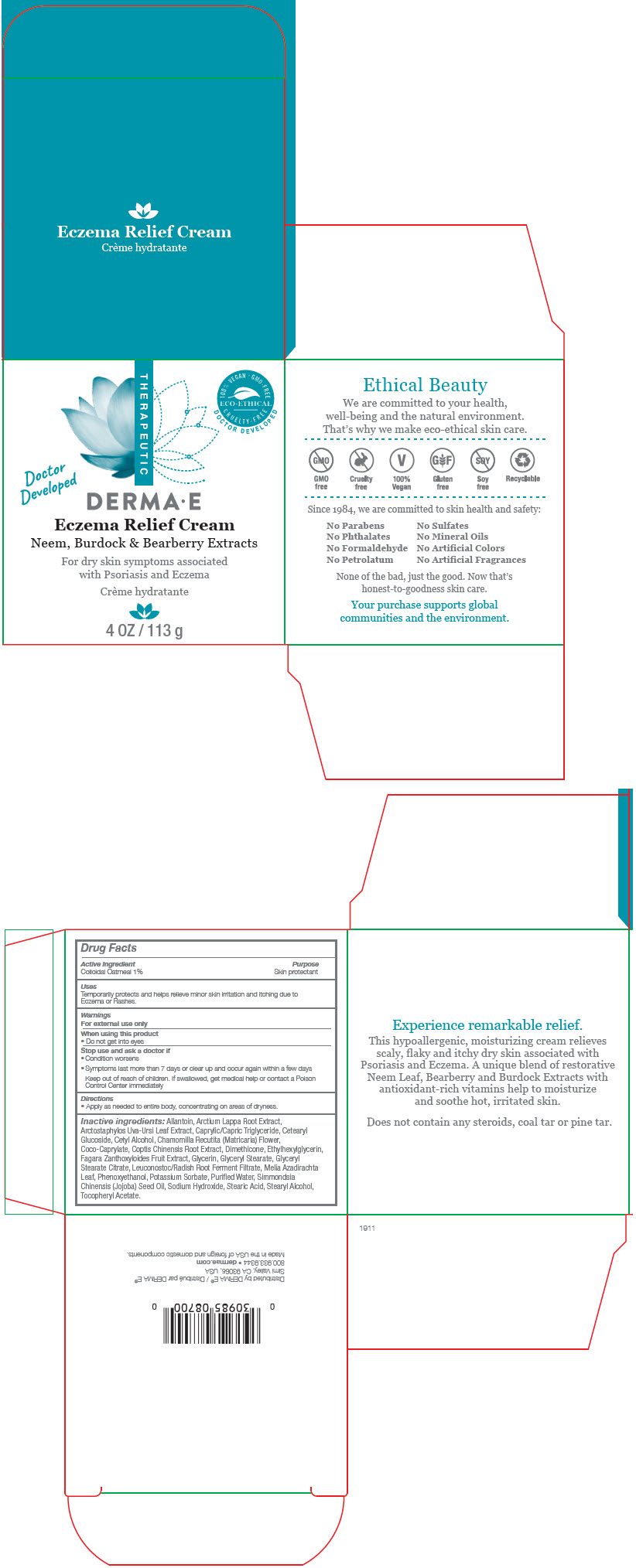 DRUG LABEL: Derma-e Eczema Relief
NDC: 51326-870 | Form: CREAM
Manufacturer: Topiderm, Inc
Category: otc | Type: HUMAN OTC DRUG LABEL
Date: 20200819

ACTIVE INGREDIENTS: OATMEAL 0.01 g/1 g
INACTIVE INGREDIENTS: ALLANTOIN; ARCTIUM LAPPA ROOT; ARCTOSTAPHYLOS UVA-URSI LEAF; MEDIUM-CHAIN TRIGLYCERIDES; CETEARYL GLUCOSIDE; CETYL ALCOHOL; MATRICARIA CHAMOMILLA FLOWERING TOP; COCO-CAPRYLATE; COPTIS CHINENSIS ROOT; DIMETHICONE; ETHYLHEXYLGLYCERIN; GLYCERIN; GLYCERYL MONOSTEARATE; GLYCERYL STEARATE CITRATE; LEUCONOSTOC/RADISH ROOT FERMENT FILTRATE; AZADIRACHTA INDICA LEAF; PHENOXYETHANOL; POTASSIUM SORBATE; WATER; JOJOBA OIL; SODIUM HYDROXIDE; STEARIC ACID; STEARYL ALCOHOL; .ALPHA.-TOCOPHEROL ACETATE

Derma-e Eczema Relief Cream

Drug Facts

Active Ingredient

Colloidal Oatmeal 1%

Purpose

Skin protectant

Uses

Temporarily protects and helps relieve minor skin irritation and itching due to Eczema or Rashes.

Warnings

For external use only

When using this product

- Do not get into eyes

Stop use and ask a doctor if

- Condition worsens
- Symptoms last more than 7 days or clear up and occur again within a few days

Keep out of reach of children. If swallowed, get medical help or contact a Poison Control Center immediately

Directions

- Apply as needed to entire body, concentrating on areas of dryness.

Inactive ingredients

Allantoin, Arctium Lappa Root Extract, Arctostaphylos Uva-Ursi Leaf Extract, Caprylic/Capric Triglyceride, Cetearyl Glucoside, Cetyl Alcohol, Chamomilla Recutita (Matricaria) Flower, Coco-Caprylate, Coptis Chinensis Root Extract, Dimethicone, Ethylhexylglycerin, Fagara Zanthoxyloides Fruit Extract, Glycerin, Glyceryl Stearate, Glyceryl Stearate Citrate, Leuconostoc/Radish Root Ferment Filtrate, Melia Azadirachta Leaf, Phenoxyethanol, Potassium Sorbate, Purifed Water, Simmondsia Chinensis (Jojoba) Seed Oil, Sodium Hydroxide, Stearic Acid, Stearyl Alcohol, Tocopheryl Acetate.

Distributed by DERMA E®
Simi Valley, CA 93065, USA

PRINCIPAL DISPLAY PANEL - 113 g Jar Box

THERAPEUTIC

100% VEGAN ∙ GMO-FREE
ECO-ETHICAL
CRUELTY-FREE
DOCTOR DEVELOPED

DOCTOR
DEVELOPED

DERMA∙E

Eczema Relief Cream

Neem, Burdock & Bearberry Extracts

For dry skin symptoms associated
with Psoriasis and Eczema

4 OZ / 113 g